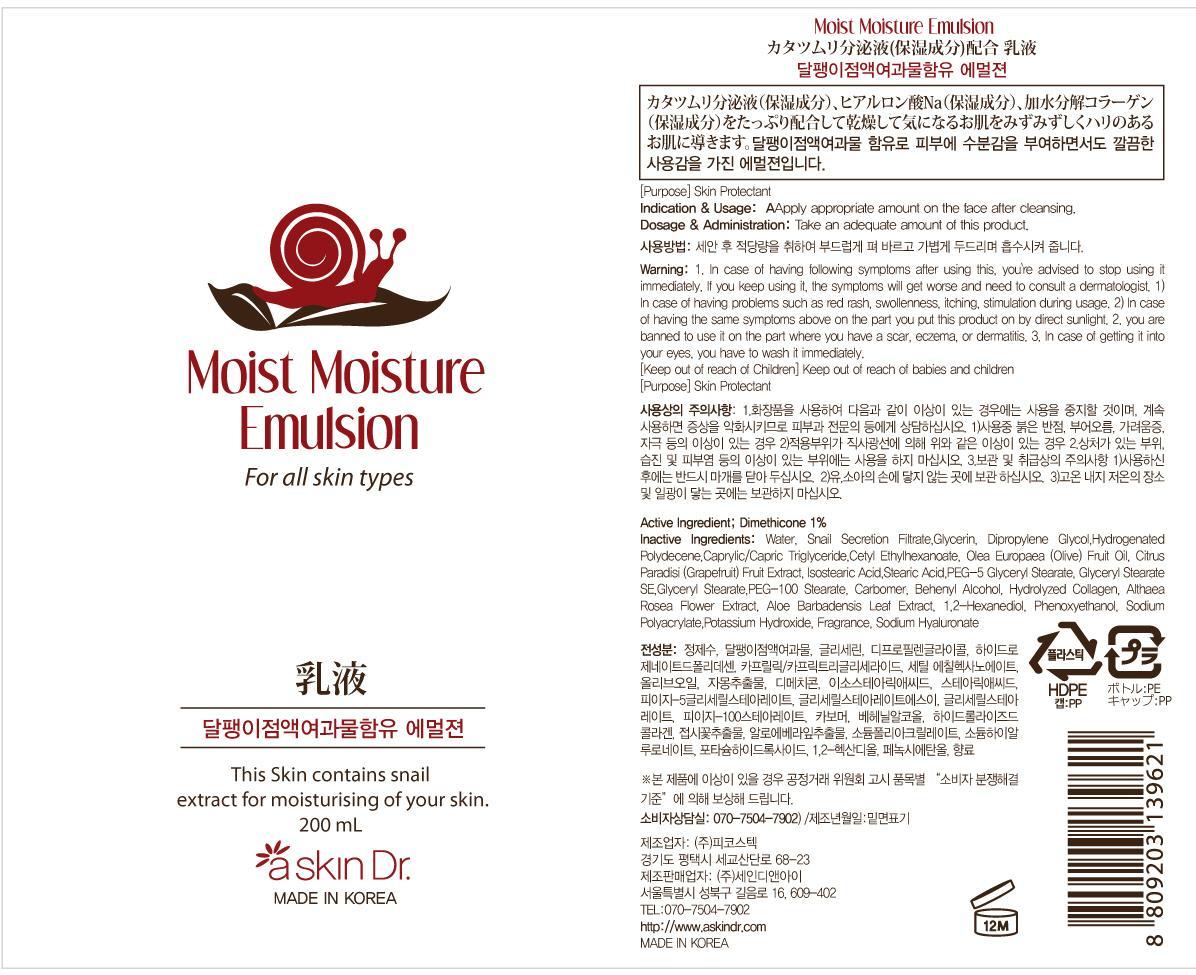 DRUG LABEL: MOIST MOISTURE
NDC: 69072-090 | Form: EMULSION
Manufacturer: Seindni Co.,ltd
Category: otc | Type: HUMAN OTC DRUG LABEL
Date: 20190530

ACTIVE INGREDIENTS: Dimethicone 2 mg/200 mL
INACTIVE INGREDIENTS: Water; Glycerin

ACTIVE INGREDIENT

Active Ingredients: Dimethicone 1%

INACTIVE INGREDIENT

Inactive Ingredients:
Water, Snail Secretion Filtrate, Glycerin, Dipropylene Glycol,Hydrogenated Polydecene,Caprylic/Capric Triglyceride,Cetyl Ethylhexanoate,Olea Europaea (Olive) Fruit Oil,Citrus Paradisi (Grapefruit) Fruit Extract, Isostearic Acid,Stearic Acid,PEG-5 Glyceryl Stearate,Glyceryl Stearate SE,Glyceryl Stearate,PEG -100 Stearate,Carbomer,Behenyl Alcohol,Hydrolyzed Collagen,Althaea Rosea Flower Extract,Aloe Barbadensis Leaf Extract,1,2-Hexanediol,Phenoxyethanol,Sodium Polyacrylate,Potassium Hydroxide,Fragrance,Sodium Hyaluronate

PURPOSE

Purpose: Skin Protectant

WARNINGS

Warning:
1. In case of having following symptoms after using this, you're advised to stop using it immediately. If you keep using it, the symptoms will get worse and need to consult a dermatologist. 1) In case of having problems such as red rash, swollenness, itching, stimulation during usage. 2) In case of having the same symptoms above on the part you put this product on by direct sunlight. 2. you are banned to use it on the part where you have a scar, eczema, or dermatitis. 3. In case of getting it into your eyes, you have to wash it immediately.

Keep out of reach of children: Keep out of reach of babies and children

INDICATIONS AND USAGE

Indication and Usage: Apply appropriate amount on the face after cleansing.

Dosage and Administration : Take an adequate amount of this product.